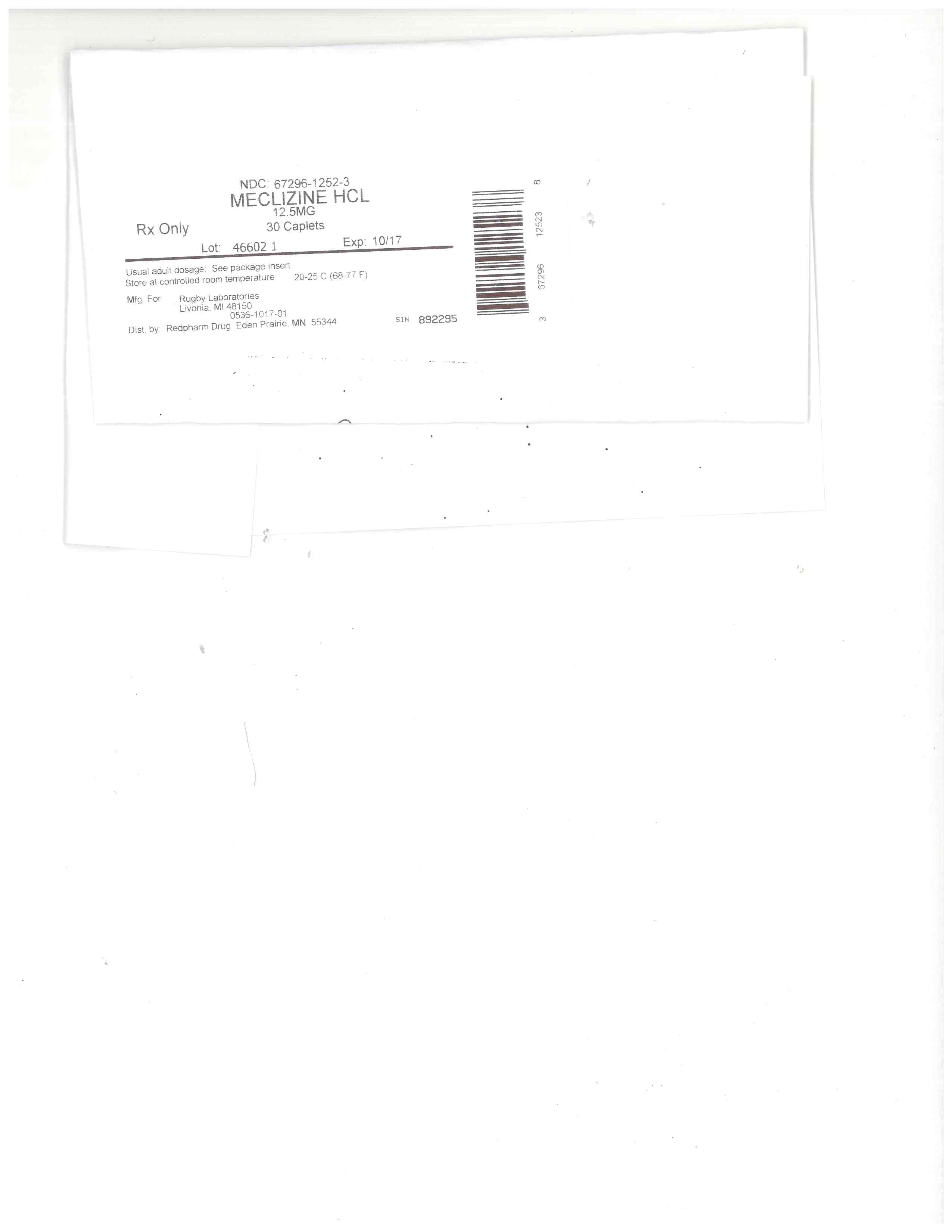 DRUG LABEL: Rugby
NDC: 67296-1252 | Form: TABLET
Manufacturer: RedPharm Drug, Inc.
Category: otc | Type: HUMAN OTC DRUG LABEL
Date: 20140307

ACTIVE INGREDIENTS: MECLIZINE HYDROCHLORIDE 12.5 mg/1 1
INACTIVE INGREDIENTS: MAGNESIUM STEARATE; CELLULOSE, MICROCRYSTALLINE; SILICON DIOXIDE; STEARIC ACID; CROSCARMELLOSE SODIUM; CALCIUM PHOSPHATE, DIBASIC, DIHYDRATE; SODIUM SULFATE

SPL UNCLASSIFIED SECTION

Drug Facts

ACTIVE INGREDIENT

Active ingredient (in each caplet)

Meclizine HCl, USP 12.5 mg

PURPOSE

Antiemetic

INDICATIONS & USAGE

Uses

prevents and treats nausea, vomiting or dizziness due to motion sickness

WARNINGS

Do not use in children under 12 years of age unless directed by a doctor

Ask a doctor before use if you have

glaucoma
a breathing problem such as emphysema or chronic bronchitis
trouble urinating due to an enlarged prostate gland

Ask a doctor or pharmacist before use if you are taking sedatives or tranquilizers.

When using this product

may cause drowsiness
alcohol, sedatives, and tranquilizers may increase drowsiness
avoid alcoholic drinks
use caution when driving a motor vehicle or operating machinery

If pregnant or breast-feeding, ask a health professional before use.

Keep out of reach of children.

In case of overdose, get medical help or contact the poison control center immediately.

DOSAGE & ADMINISTRATION

Directions

Dosage should be taken one hour before travel starts.
Adults and children 12 years of age and older: take 2-4 caplets once daily, or as directed by a doctor
Children under 12 years: do not give this product to children under 12 years of age unless directed by a doctor

STORAGE AND HANDLING

Other information

Each Caplet Contains: Calcium 25 mg
store at room temperature in a dry place
Keep lid tightly closed

INACTIVE INGREDIENT

Inactive ingredients

croscarmellose sodium, dicalcium phosphate dihydrate, magnesium stearate, microcrystalline cellulose, silicon dioxide, sodium sulfate, stearic acid.

QUESTIONS

Questions or comments?

call 1-800-645-2158

OTHER SAFETY INFORMATION

TAMPER EVIDENT: DO NOT USE IF IMPRINTED SAFETY SEAL UNDER CAP IS BROKEN OR MISSING

SPL UNCLASSIFIED SECTION

Distributed by: Rugby Laboratories

17177 N. Laurel Park Drive, Suite 233

Livonia, MI 48152

www.rugbylaboratories.com

OTC KEEP OUT OF REACH OF CHILDREN

KEEP OUT OF THE REACH OF CHILDREN